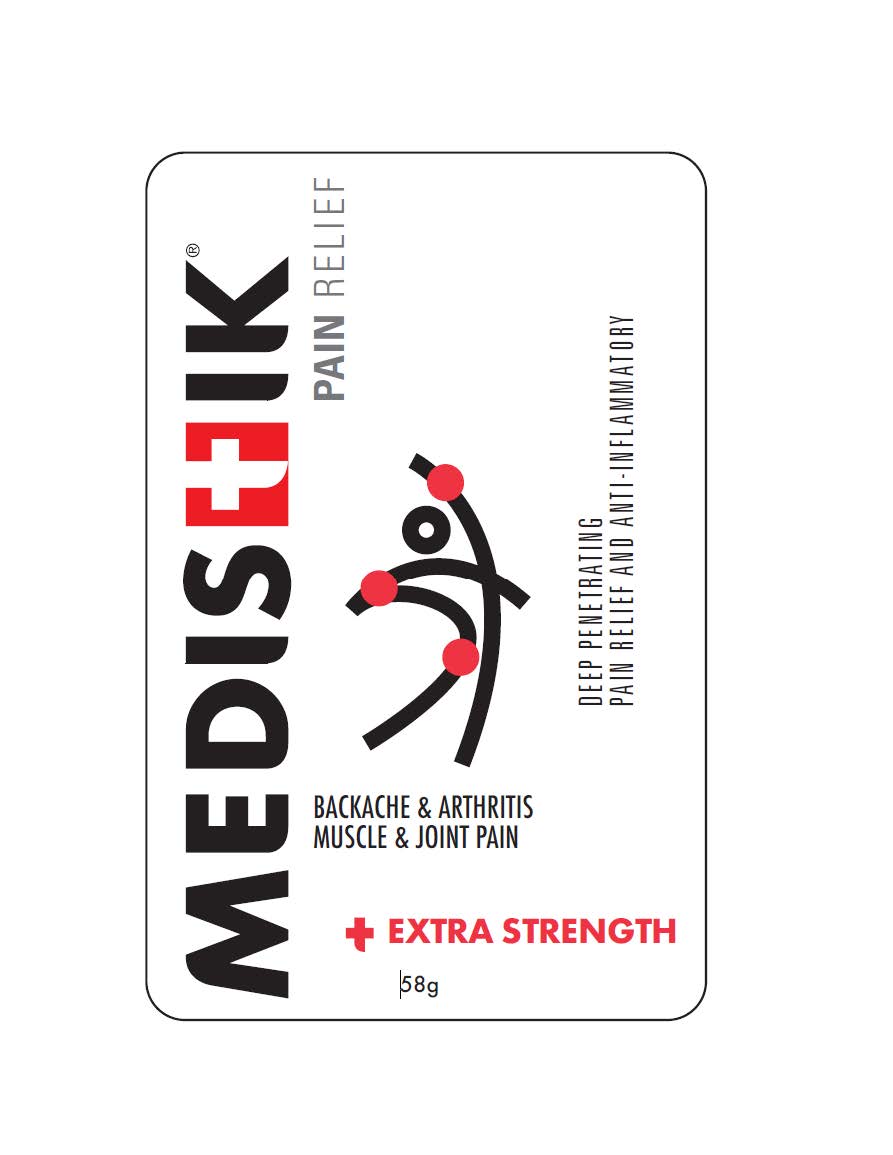 DRUG LABEL: MEDISTIK PROFESSIONAL DUAL ACTION
NDC: 50231-221 | Form: STICK
Manufacturer: Natureteq Inc.
Category: otc | Type: HUMAN OTC DRUG LABEL
Date: 20260227

ACTIVE INGREDIENTS: MENTHOL 15 g/100 g; METHYL SALICYLATE 30 g/100 g; EUCALYPTUS GLOBULUS LEAF 1 g/100 g
INACTIVE INGREDIENTS: BUTYLATED HYDROXYTOLUENE; HYDROGENATED CASTOR OIL; OLEIC ACID; PARAFFIN; PETROLATUM

Natureteq (as PLD) - MEDISTIK DUAL ACTION STICK (50231-221)

ACTIVE INGREDIENTS

Menthol 15%

Methyl Salicylate 30%

Eucaluptus Oil 1%

PURPOSE

Topical Analgesic

USES

MEDISTIK™ DUAL provides temporary soothing relief of sore muscles associated with strains and sprains, backaches, lumbago, pain of tendons and/or ligaments as well as arthritic or rheumatic pain

WARNINGS

For external use only. The application of external heat may cause skin irritation or burn. Avoid contact with eyes and broken skin. Do not bandage. DO NOT USE IF ALLERGIC TO SALICYLATES OR IF TAKING ANTICOAGULANT MEDICATIONS. Stop use and consult a physician if condition worsens, rash or irritation develops, or if symptoms persist for more than 7 days or clear up and recur in a few days.

DIRECTIONS

For use on adults and children over 12 years of age. Apply generously to the affected area using hands-free applicator. Use 3 to 4 times per day as required. A stinging or burning sensation will be experienced during the first few minutes as the formula begins working. For arthritis or muscle pain of the hands, retain for at least 10 minutes then wash hands.

INACTIVE INGREDIENTS

Paraffin Wax, Hydrogenated Castor Oil, White Petrolatum, Oleic Acid 700, BHT

KEEP OUT OF REACH OF CHILDREN